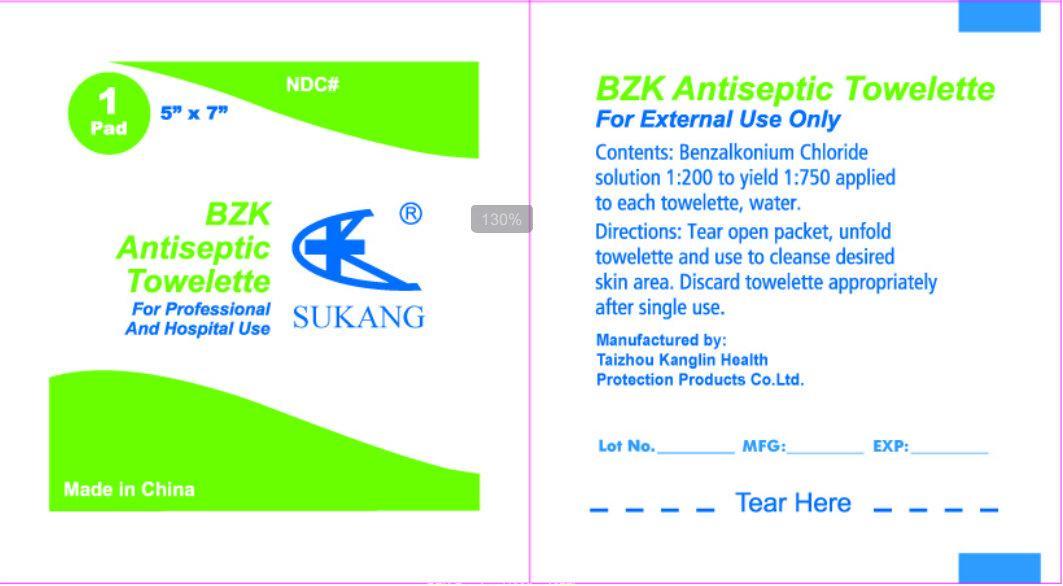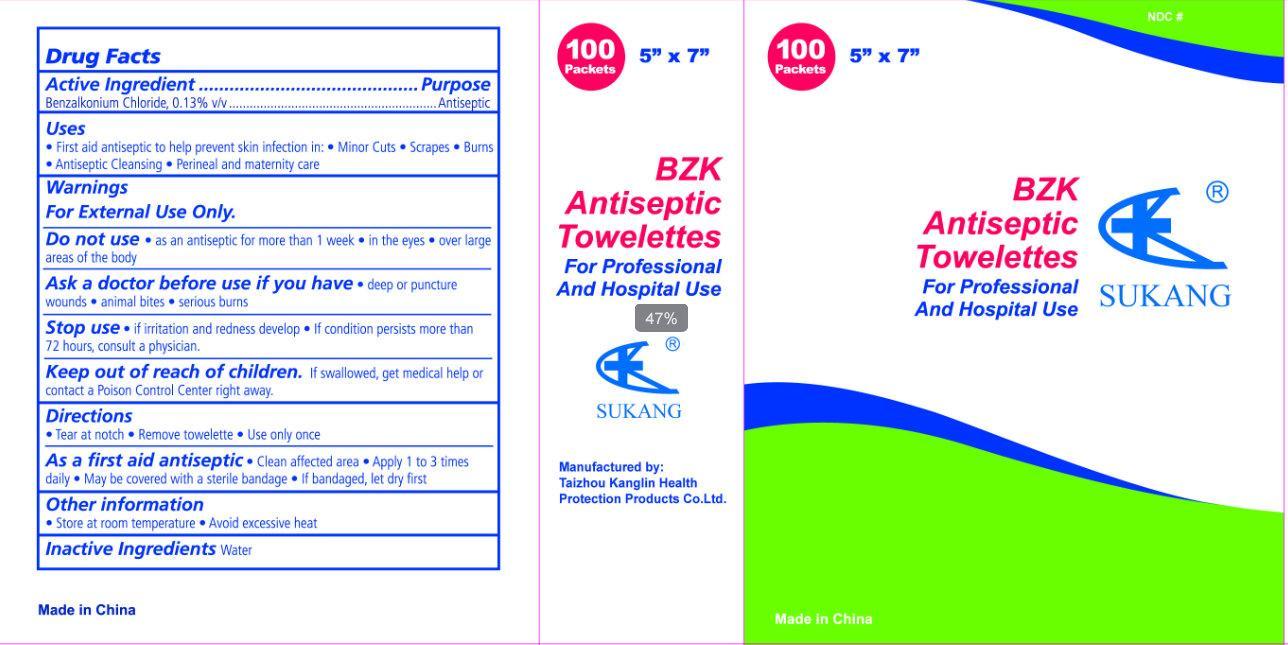 DRUG LABEL: SUKANG BZK Antiseptic Towelette
NDC: 22408-001 | Form: LIQUID
Manufacturer: Taizhou Kanglin Health Protection Products Co Ltd
Category: otc | Type: HUMAN OTC DRUG LABEL
Date: 20130213

ACTIVE INGREDIENTS: BENZALKONIUM CHLORIDE 0.13 g/100 g
INACTIVE INGREDIENTS: WATER

SUKANG BZK Antiseptic Towelette

Active Ingredient

Benzalkonium Chloride, 0.13% v/v

Purpose

Antiseptic

Uses

First aid antiseptic to help prevent skin infection in: minor cuts, scrapes, burns

Antiseptic cleansing

Perineal and maternity care

Warnings

For external use only.

Do not use

- as an antiseptic for more than 1 week
- in the eyes
- over large areas of the body

Ask a doctor before use if you have

- deep or puncture wounds
- animal bites
- serious burns

Stop use

- if irritation and redness develops
- if condition persists for more than 72 hours, consult a physician

Keep out of reach of children

- If swallowed, get medical help or contact a Poison Control Center right away.

Directions

Tear at notch

Remove towelette

Use only once

As a first aid antiseptic

Clean affected area

Apply 1 to 3 times daily

May be covered with a sterile bandage

If bandaged, let dry first

Other Information

- Store at room temperature
- Avoid excessive heat

Inactive Ingredient

water